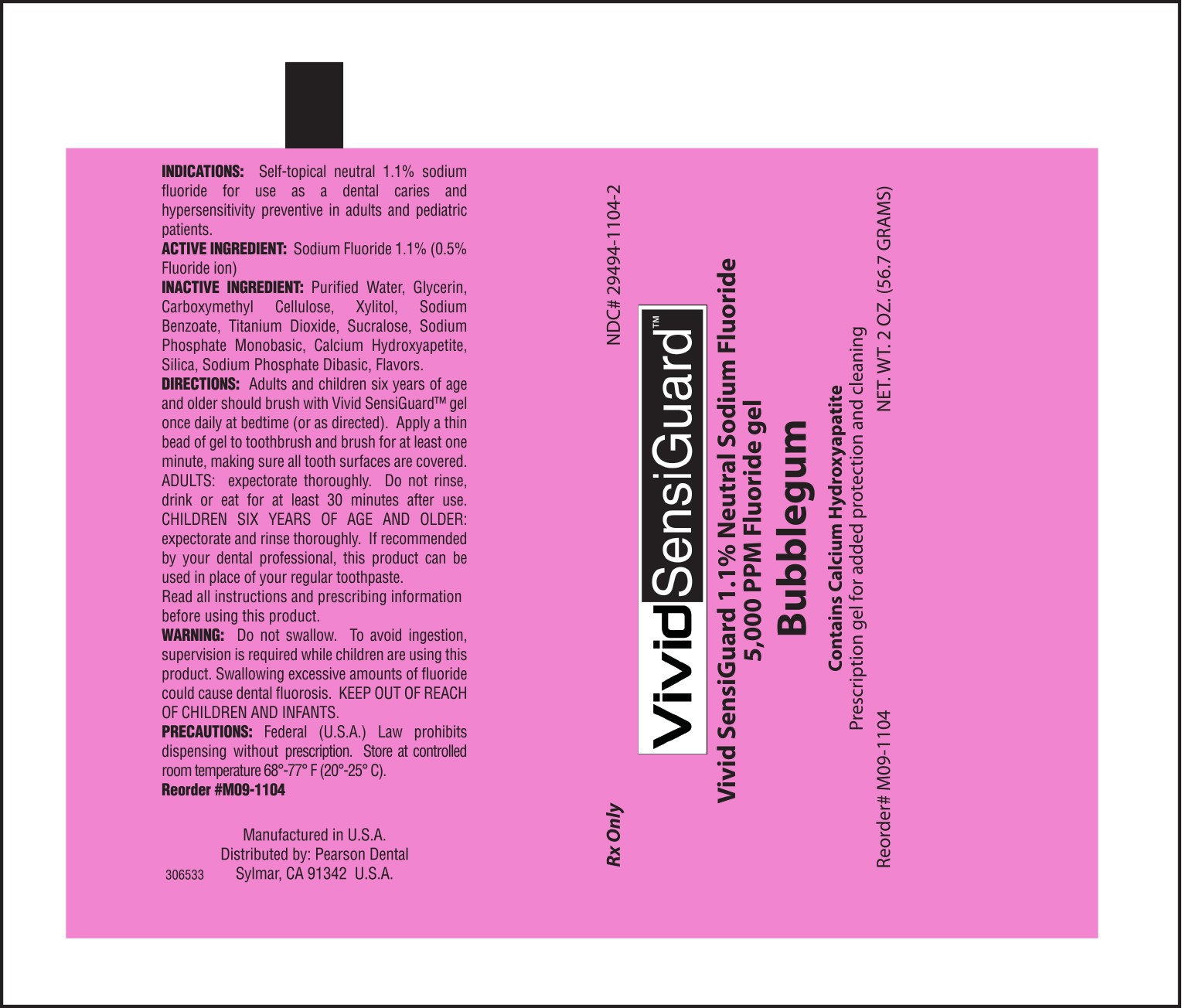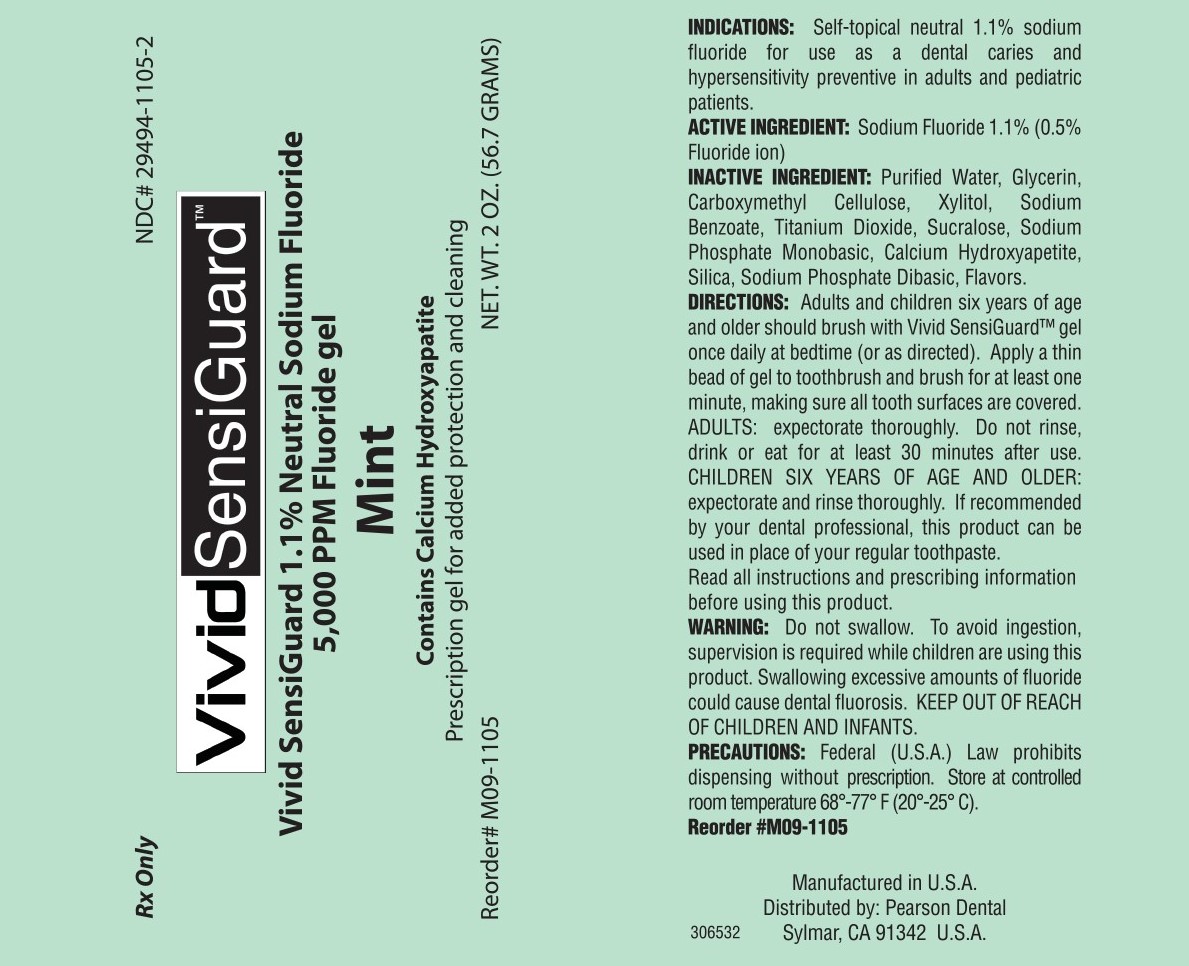 DRUG LABEL: VividSensiGuard
NDC: 29494-1105 | Form: GEL, DENTIFRICE
Manufacturer: Pearson Dental Supply Co.
Category: prescription | Type: HUMAN PRESCRIPTION DRUG LABEL
Date: 20160707

ACTIVE INGREDIENTS: SODIUM FLUORIDE 11 mg/1 g
INACTIVE INGREDIENTS: XYLITOL; CARBOXYMETHYLCELLULOSE; TRIBASIC CALCIUM PHOSPHATE; SILICON DIOXIDE; SODIUM PHOSPHATE, DIBASIC; GLYCERIN; SODIUM BENZOATE; SUCRALOSE; SODIUM PHOSPHATE, MONOBASIC; WATER; TITANIUM DIOXIDE

Active Ingredient

Sodium Fluoride 1.1%

(0.5% Fluoride Ion)

Indications

Self-topical neutral 1.1% sodium fluoride for use as a dental caries and hypersensitivity preventative in adults and pediatric patients.

Directions

Adults and children six years of age and older should brush with Vivid SensiGuard™ gel once at bedtime (or as directed). Apply a thin bead of gel to toothbrush and brush for at least one minute, making sure all tooth surfaces are covered. ADULTS: expectorate thoroughly. Do not rinse, drink or eat for at least 30 minutes after use. CHILDREN SIX YEARS OF AGE AND OLDER: expectorate and rinse thoroughly. If recommended by your dental professional, this product can be used in place of your regular toothpaste. Read all instructions and prescribing information before using this product.

Warning

Do not swallow. To avoid ingestion, supervision is required while children are using this product. Swallowing excessive amounts of fluoride could cause dental fluorosis. KEEP OUT OF REACH OF CHILDREN AND INFANTS.

Precautions

Federal (U.S.A.) Law prohibits dispensing without prescription. Store at controlled room temperature 68º - 77º F (20ºC - 25ºC).
Reorder # M09-1104

Reorder # M09-1105
Manufactured in U.S.A.

Distributed by: Pearson Dental

Sylmar, CA 91342 U.S.A.

Inactive Ingredients

Purified Water, Glycerin, Carboxymethyl Cellulose, Xylitol, Sodium Benzoate, Titanium Dioxide, Sucralose, Sodium Phosphate Monobasic, Calcium Hydroxyapetite, Silica, Sodium Phosphate Dibasic, Flavors.

VIVIDSENSIGUARD

bubble gum.jpg

mint.jpg